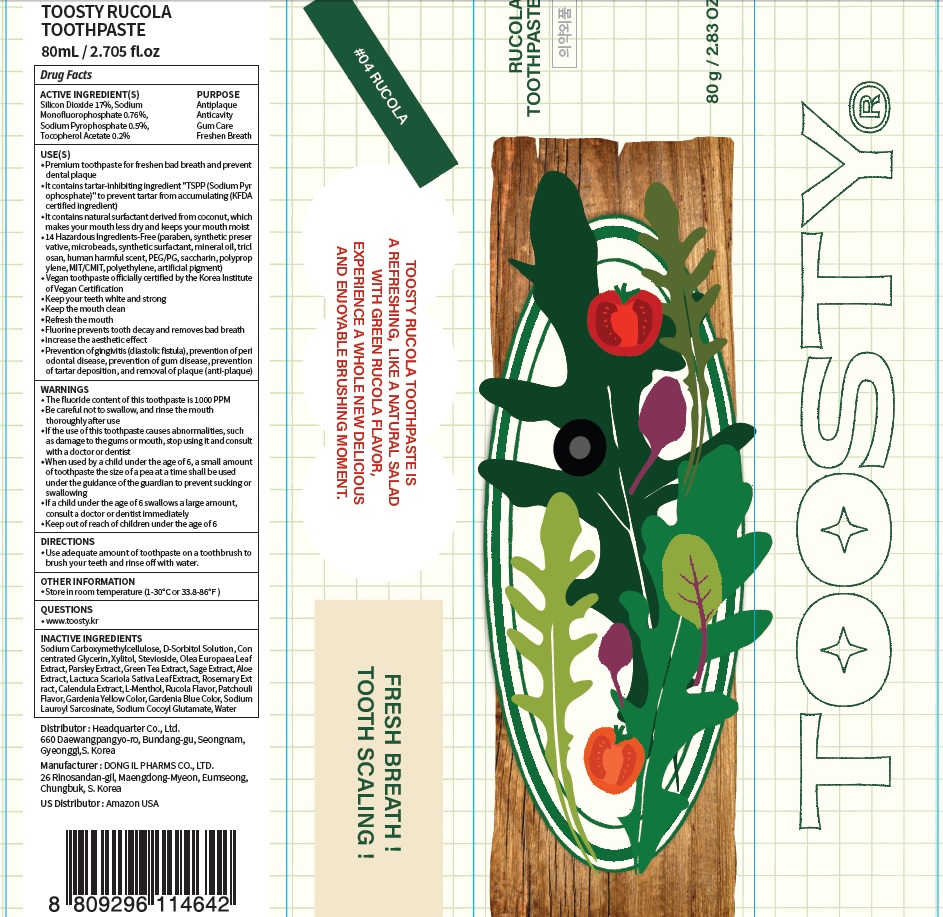 DRUG LABEL: Toosty Rucola Toothpaste
NDC: 82662-020 | Form: PASTE, DENTIFRICE
Manufacturer: Headquarter Co., Ltd
Category: otc | Type: HUMAN OTC DRUG LABEL
Date: 20230726

ACTIVE INGREDIENTS: Silicon Dioxide 17.0 g/100 g; Sodium Monofluorophosphate 0.76 g/100 g; Sodium Pyrophosphate 0.5 g/100 g; .ALPHA.-TOCOPHEROL ACETATE 0.2 g/100 g
INACTIVE INGREDIENTS: CARBOXYMETHYLCELLULOSE SODIUM, UNSPECIFIED; SORBITOL; Glycerin

ACTIVE INGREDIENTS

Silicon Dioxide 17%
Sodium Monofluorophosphate 0.76%
Sodium Pyrophosphate 0.5%
Tocopherol Acetate 0.2%

INACTIVE INGREDIENTS

Sodium Carboxymethylcellulose, D-Sorbitol Solution, Concentrated Glycerin, Xylitol, Stevioside, Olea Europaea Leaf Extract, Parsley Extract, Green Tea Extract, Sage Extract, Aloe Extract, Lactuca Scariola Sativa Leaf Extract, Rosemary Extract, Calendula Extract, L-Menthol, Rucola Flavor, Patchouli Flavor, Gardenia Yellow Color, Gardenia Blue Color, Sodium Lauroyl Sarcosinate, Sodium Cocoyl Glutamate, Water

PURPOSE

Antiplaque
Anticavity
Gum Care
Freshen Breath

WARNINGS

■ The fluoride content of this toothpaste is 1000 PPM
■ Be careful not to swallow, and rinse the mouth thoroughly after use
■ If the use of this toothpaste causes abnormalities, such as damage to the gums or mouth, stop using it and consult with a doctor or dentist
■ When used by a child under the age of 6, a small amount of toothpaste the size of a pea at a time shall be used under the guidance of the guardian to prevent sucking or swallowing
■ If a child under the age of 6 swallows a large amount, consult a doctor or dentist immediately
■ Keep out of reach of children under the age of 6

Keep out of reach of children under the age of 6

Uses

■ Premium toothpaste for freshen bad breath and prevent dental plaque
■ It contains tartar-inhibiting ingredient "TSPP (Sodium Pyrophosphate)" to prevent tartar from accumulating (KFDA certified ingredient)
■ It contains natural surfactant derived from coconut, which makes your mouth less dry and keeps your mouth moist
■ 14 Hazardous Ingredients-Free (paraben, synthetic preservative, microbeads, synthetic surfactant, mineral oil, triclosan, human harmful scent, PEG/PG, saccharin, polypropylene, MIT/CMIT, polyethylene, artificial pigment)
■ Vegan toothpaste officially certified by the Korea Institute of Vegan Certification
■ Keep your teeth white and strong
■ Keep the mouth clean
■ Refresh the mouth
■ Fluorine prevents tooth decay and removes bad breath
■ increase the aesthetic effect
■ Prevention of gingivitis (diastolic fistula), prevention of periodontal disease, prevention of gum disease, prevention of tartar deposition, and removal of plaque (anti-plaque)

Directions

■ Use adequate amount of toothpaste on a toothbrush to brush your teeth and rinse off with water.

Other Information

■ Store in room temperature (1-30℃ or 33.8-86℉)

Questions

■ www.toosty.kr